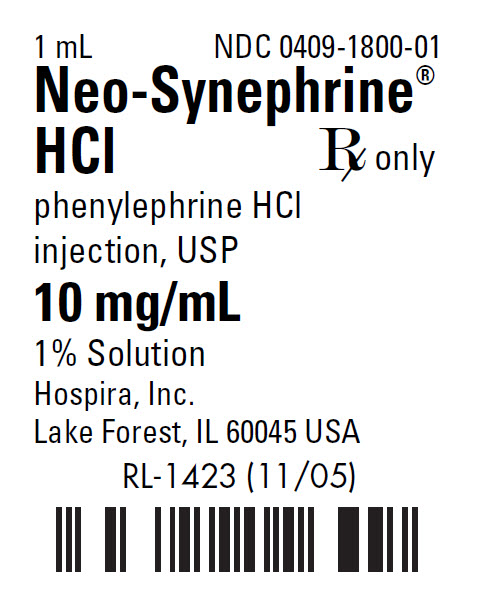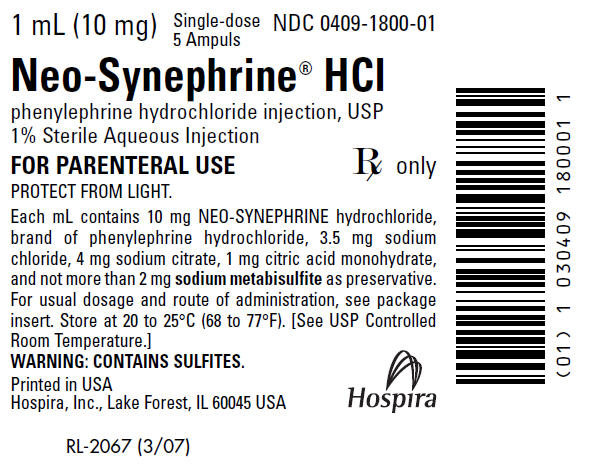 DRUG LABEL: Neo-Synephrine Hydrochloride
NDC: 0409-1800 | Form: INJECTION, SOLUTION
Manufacturer: Hospira, Inc.
Category: prescription | Type: HUMAN PRESCRIPTION DRUG LABEL
Date: 20210113

ACTIVE INGREDIENTS: PHENYLEPHRINE HYDROCHLORIDE 10 mg/1 mL
INACTIVE INGREDIENTS: SODIUM CHLORIDE 3.5 mg/1 mL; SODIUM CITRATE, UNSPECIFIED FORM 4 mg/1 mL; CITRIC ACID MONOHYDRATE 1 mg/1 mL; SODIUM METABISULFITE

Neo-Synephrine® HCl

PRINCIPAL DISPLAY PANEL - 1 mL Ampule Label

1 mL
NDC 0409-1800-01

Neo-Synephrine®
HCl

Rx only

phenylephrine HCl
injection, USP

10 mg/mL

1% Solution
Hospira, Inc.
Lake Forest, IL 60045 USA

RL-1423 (11/05)

PRINCIPAL DISPLAY PANEL - 1 mL Ampule Cello Pack Label

1 mL (10 mg)
Single-dose
5 Ampuls
NDC 0409-1800-01

Neo-Synephrine® HCl
phenylephrine hydrochloride injection, USP
1% Sterile Aqueous Injection

FOR PARENTERAL USE
Rx only

PROTECT FROM LIGHT.

Each mL contains 10 mg NEO-SYNEPHRINE hydrochloride,
brand of phenylephrine hydrochloride, 3.5 mg sodium
chloride, 4 mg sodium citrate, 1 mg citric acid monohydrate,
and not more than 2 mg sodium metabisulfite as preservative.
For usual dosage and route of administration, see package
insert. Store at 20 to 25°C (68 to 77°F). [See USP Controlled
Room Temperature.]
WARNING: CONTAINS SULFITES.

Printed in USA
Hospira, Inc., Lake Forest, IL 60045 USA
Hospira

RL-2067 (3/07)